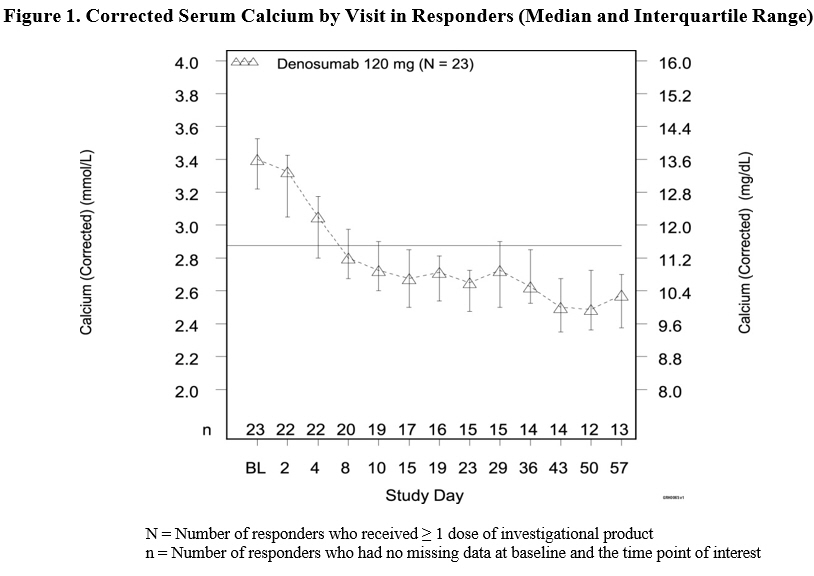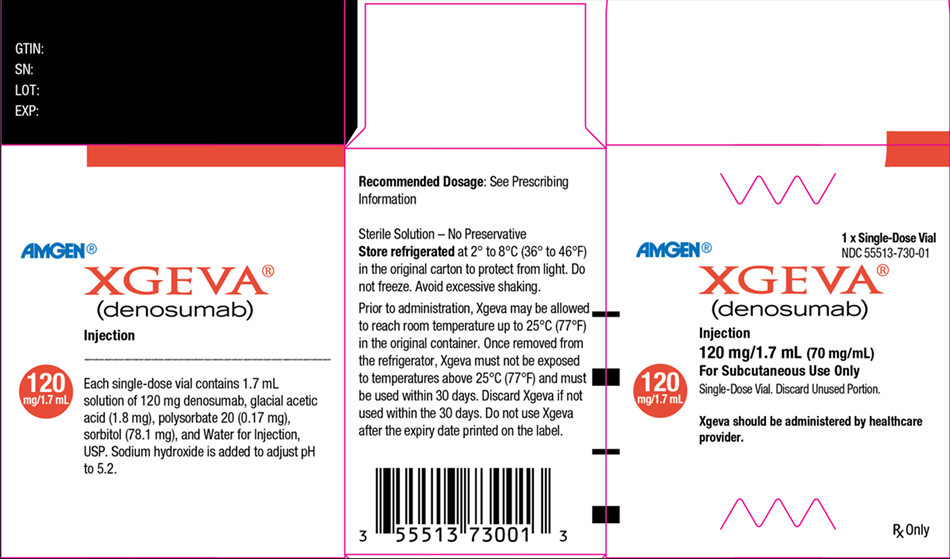 DRUG LABEL: XGEVA
NDC: 55513-730 | Form: INJECTION
Manufacturer: Amgen, Inc
Category: prescription | Type: HUMAN PRESCRIPTION DRUG LABEL
Date: 20250916

ACTIVE INGREDIENTS: DENOSUMAB 120 mg/1.7 mL
INACTIVE INGREDIENTS: SODIUM ACETATE 1.8 mg/1.7 mL; POLYSORBATE 20 0.17 mg/1.7 mL; SORBITOL 78.1 mg/1.7 mL; WATER; SODIUM HYDROXIDE

HIGHLIGHTS OF PRESCRIBING INFORMATION

These highlights do not include all the information needed to use XGEVA® safely and effectively. See full prescribing information for XGEVA.
Xgeva (denosumab) injection, for subcutaneous use
Initial U.S. Approval: 2010

RECENT MAJOR CHANGES

Dosage and Administration (2.1) | 05/2025

1 INDICATIONS AND USAGE

Xgeva is a RANK ligand (RANKL) inhibitor indicated for:

- Prevention of skeletal-related events in patients with multiple myeloma and in patients with bone metastases from solid tumors. (1.1)
- Treatment of adults and skeletally mature adolescents with giant cell tumor of bone that is unresectable or where surgical resection is likely to result in severe morbidity. (1.2, 14.3)
- Treatment of hypercalcemia of malignancy refractory to bisphosphonate therapy. (1.3)

2 DOSAGE AND ADMINISTRATION

- Xgeva should be administered by a healthcare provider. (2.1)
- Xgeva is intended for subcutaneous route only and should not be administered intravenously, intramuscularly, or intradermally. (2.1)
- Multiple Myeloma and Bone Metastasis from Solid Tumors: Administer 120 mg every 4 weeks as a subcutaneous injection in the upper arm, upper thigh, or abdomen. (2.2)
- Giant Cell Tumor of Bone: Administer 120 mg every 4 weeks with additional 120 mg doses on Days 8 and 15 of the first month of therapy. Administer subcutaneously in the upper arm, upper thigh, or abdomen. (2.3)
- Administer calcium and vitamin D as necessary to treat or prevent hypocalcemia. (2.2, 2.3)
- Hypercalcemia of Malignancy: Administer 120 mg every 4 weeks with additional 120 mg doses on Days 8 and 15 of the first month of therapy. Administer subcutaneously in the upper arm, upper thigh, or abdomen. (2.4)

3 DOSAGE FORMS AND STRENGTHS

- Injection: 120 mg/1.7 mL (70 mg/mL) solution in a single-dose vial (3)

4 CONTRAINDICATIONS

- Hypocalcemia (4.1)
- Known clinically significant hypersensitivity to Xgeva or denosumab products (4.2)

5 WARNINGS AND PRECAUTIONS

- Drug Products with Same Active Ingredient: Patients receiving Xgeva should not receive other denosumab products concomitantly. (5.1)
- Hypersensitivity reactions including anaphylaxis may occur. Discontinue permanently if a clinically significant reaction occurs. (5.2)
- Hypocalcemia: Xgeva can cause severe symptomatic hypocalcemia, and fatal cases have been reported. Correct hypocalcemia prior to initiating Xgeva. Monitor calcium levels during therapy, especially in the first weeks of initiating therapy, and adequately supplement all patients with calcium and vitamin D. (5.3)
- Osteonecrosis of the jaw (ONJ) has been reported in patients receiving Xgeva. Perform an oral examination prior to starting Xgeva. Monitor for symptoms. Avoid invasive dental procedures during treatment with Xgeva. (5.4)
- Atypical femoral fracture: Evaluate patients with thigh or groin pain to rule out a femoral fracture. (5.5)
- Hypercalcemia Following Treatment Discontinuation in Patients with Giant Cell Tumor of Bone and in Patients with Growing Skeletons: Monitor patients for signs and symptoms of hypercalcemia, and manage as clinically appropriate. (5.6, 8.4)
- Multiple Vertebral Fractures (MVF) Following Treatment Discontinuation: When Xgeva treatment is discontinued, evaluate the individual patient’s risk for vertebral fractures. (5.7)
- Embryo-Fetal Toxicity: Can cause fetal harm. Advise females of reproductive potential of potential risk to the fetus and to use effective contraception. (5.8, 8.1, 8.3)

6 ADVERSE REACTIONS

- Bone Metastasis from Solid Tumors: Most common adverse reactions (≥ 25%) were fatigue/asthenia, hypophosphatemia, and nausea. (6.1)
- Multiple Myeloma: Most common adverse reactions (≥ 10%) were diarrhea, nausea, anemia, back pain, thrombocytopenia, peripheral edema, hypocalcemia, upper respiratory tract infection, rash, and headache. (6.1)
- Giant Cell Tumor of Bone: Most common adverse reactions (≥ 10%) were arthralgia, headache, nausea, back pain, fatigue, and pain in extremity. (6.1)
- Hypercalcemia of Malignancy: Most common adverse reactions (> 20%) were nausea, dyspnea, decreased appetite, headache, peripheral edema, vomiting, anemia, constipation, and diarrhea. (6.1)

To report SUSPECTED ADVERSE REACTIONS, contact Amgen Inc. at 1-800-77-AMGEN (1-800-772-6436) or FDA at 1-800-FDA-1088 or www.fda.gov/medwatch.

8 USE IN SPECIFIC POPULATIONS

- Pediatric patients: Recommended only for treatment of skeletally mature adolescents with giant cell tumor of bone. (8.4)
- Renal impairment: Patients with creatinine clearance less than 30 mL/min or receiving dialysis are at risk for hypocalcemia. Adequately supplement with calcium and vitamin D. (8.6)

FULL PRESCRIBING INFORMATION

1 INDICATIONS AND USAGE

1.1 Multiple Myeloma and Bone Metastasis from Solid Tumors

Xgeva is indicated for the prevention of skeletal-related events in patients with multiple myeloma and in patients with bone metastases from solid tumors.

1.2 Giant Cell Tumor of Bone

Xgeva is indicated for the treatment of adults and skeletally mature adolescents with giant cell tumor of bone that is unresectable or where surgical resection is likely to result in severe morbidity [see Clinical Trials (14.2)].

1.3 Hypercalcemia of Malignancy

Xgeva is indicated for the treatment of hypercalcemia of malignancy refractory to bisphosphonate therapy.

2 DOSAGE AND ADMINISTRATION

2.1 Important Administration Instructions

Xgeva should be administered by a healthcare provider.

Xgeva is intended for subcutaneous route only and should not be administered intravenously, intramuscularly, or intradermally.

2.2 Multiple Myeloma and Bone Metastasis from Solid Tumors

The recommended dose of Xgeva is 120 mg administered as a subcutaneous injection every 4 weeks in the upper arm, upper thigh, or abdomen.

Administer calcium and vitamin D as necessary to treat or prevent hypocalcemia [see Warnings and Precautions (5.3)].

2.3 Giant Cell Tumor of Bone

The recommended dose of Xgeva is 120 mg administered every 4 weeks with additional 120 mg doses on Days 8 and 15 of the first month of therapy. Administer subcutaneously in the upper arm, upper thigh, or abdomen.

Administer calcium and vitamin D as necessary to treat or prevent hypocalcemia [see Warnings and Precautions (5.3)].

2.4 Hypercalcemia of Malignancy

The recommended dose of Xgeva is 120 mg administered every 4 weeks with additional 120 mg doses on Days 8 and 15 of the first month of therapy. Administer subcutaneously in the upper arm, upper thigh, or abdomen.

2.5 Preparation and Administration

Parenteral drug products should be inspected visually for particulate matter and discoloration prior to administration whenever solution and container permit. Xgeva is a clear, colorless to pale yellow solution that may contain trace amounts of translucent to white proteinaceous particles. Do not use if the solution is discolored or cloudy or if the solution contains many particles or foreign particulate matter.

Prior to administration, Xgeva may be removed from the refrigerator and brought to room temperature up to 25°C (77°F) by standing in the original container. This generally takes 15 to 30 minutes. Do not warm Xgeva in any other way [see How Supplied/Storage and Handling (16)].

Use a 27-gauge needle to withdraw and inject the entire contents of the vial. Do not re-enter the vial. Discard vial after single entry.

3 DOSAGE FORMS AND STRENGTHS

Injection: 120 mg/1.7 mL (70 mg/mL) clear, colorless to pale yellow solution in a single-dose vial.

4 CONTRAINDICATIONS

4.1 Hypocalcemia

Pre-existing hypocalcemia must be corrected prior to initiating therapy with Xgeva [see Warnings and Precautions (5.3)].

4.2 Hypersensitivity

Xgeva is contraindicated in patients with known clinically significant hypersensitivity to Xgeva or denosumab products [see Warnings and Precautions (5.2) and Adverse Reactions (6.2)].

5 WARNINGS AND PRECAUTIONS

5.1 Drug Products with Same Active Ingredient

Patients receiving Xgeva should not receive other denosumab products concomitantly.

5.2 Hypersensitivity

Clinically significant hypersensitivity including anaphylaxis has been reported with use of Xgeva. Reactions may include hypotension, dyspnea, upper airway edema, lip swelling, rash, pruritus, and urticaria. If an anaphylactic or other clinically significant allergic reaction occurs, initiate appropriate therapy and discontinue Xgeva therapy permanently [see Contraindications (4.2) and Adverse Reactions (6.2)].

5.3 Hypocalcemia

Xgeva can cause severe symptomatic hypocalcemia, and fatal cases have been reported. Correct pre-existing hypocalcemia prior to Xgeva treatment. Monitor calcium levels, throughout Xgeva therapy, especially in the first weeks of initiating therapy, and administer calcium, magnesium, and vitamin D as necessary. Concomitant use of calcimimetics and other drugs that can lower calcium levels may worsen hypocalcemia risk and serum calcium should be closely monitored. Advise patients to contact a healthcare provider for symptoms of hypocalcemia [see Contraindications (4.1), Adverse Reactions (6.1, 6.2), and Patient Counseling Information (17)].

An increased risk of hypocalcemia has been observed in clinical trials of patients with increasing renal dysfunction, most commonly with severe dysfunction (creatinine clearance less than 30 mL/min and/or on dialysis), and with inadequate/no calcium supplementation. Monitor calcium levels and calcium and vitamin D intake [see Adverse Reactions (6.1), Use in Specific Populations (8.6), and Clinical Pharmacology (12.3)].

5.4 Osteonecrosis of the Jaw (ONJ)

Osteonecrosis of the jaw (ONJ) has been reported in patients receiving Xgeva, manifesting as jaw pain, osteomyelitis, osteitis, bone erosion, tooth or periodontal infection, toothache, gingival ulceration, or gingival erosion. Persistent pain or slow healing of the mouth or jaw after dental surgery may also be manifestations of ONJ. In clinical trials in patients with cancer, the incidence of ONJ was higher with longer duration of exposure [see Adverse Reactions (6.1)]. Seventy-nine percent of patients with ONJ had a history of tooth extraction, poor oral hygiene, or use of a dental appliance as a predisposing factor. Other risk factors for the development of ONJ include immunosuppressive therapy, treatment with angiogenesis inhibitors, systemic corticosteroids, diabetes, and gingival infections. Similarly, for Xgeva patients with multiple myeloma that developed ONJ, 58% had a history of invasive dental procedures as a predisposing factor.

Perform an oral examination and appropriate preventive dentistry prior to the initiation of Xgeva and periodically during Xgeva therapy. Advise patients regarding oral hygiene practices. Avoid invasive dental procedures during treatment with Xgeva. Consider temporary discontinuation of Xgeva therapy if an invasive dental procedure must be performed. There are no data available to suggest the optimal duration of treatment interruption.

Patients who are suspected of having or who develop ONJ while on Xgeva should receive care by a dentist or an oral surgeon. In these patients, extensive dental surgery to treat ONJ may exacerbate the condition. Clinical judgment of the treating healthcare provider should guide the management plan of each patient based on individual risk/benefit assessment.

5.5 Atypical Subtrochanteric and Diaphyseal Femoral Fracture

Atypical femoral fracture has been reported with Xgeva [see Adverse Reactions (6.1)]. These fractures can occur anywhere in the femoral shaft from just below the lesser trochanter to above the supracondylar flare and are transverse or short oblique in orientation without evidence of comminution.

Atypical femoral fractures most commonly occur with minimal or no trauma to the affected area. They may be bilateral and many patients report prodromal pain in the affected area, usually presenting as dull, aching thigh pain, weeks to months before a complete fracture occurs. A number of reports note that patients were also receiving treatment with glucocorticoids (e.g., prednisone) at the time of fracture.

During Xgeva treatment, patients should be advised to report new or unusual thigh, hip, or groin pain. Any patient who presents with thigh or groin pain should be suspected of having an atypical fracture and should be evaluated to rule out an incomplete femur fracture. Patient presenting with an atypical femur fracture should also be assessed for symptoms and signs of fracture in the contralateral limb. Interruption of Xgeva therapy should be considered, pending a risk/benefit assessment, on an individual basis.

5.6 Hypercalcemia Following Treatment Discontinuation in Patients with Giant Cell Tumor of Bone and in Patients with Growing Skeletons

Clinically significant hypercalcemia requiring hospitalization and complicated by acute renal injury has been reported in Xgeva-treated patients with giant cell tumor of bone and patients with growing skeletons. Hypercalcemia has been reported within the first year after treatment discontinuation. After treatment is discontinued, monitor patients for signs and symptoms of hypercalcemia, assess serum calcium periodically, reevaluate the patient’s calcium and vitamin D supplementation requirements and manage patients as clinically appropriate [see Adverse Reactions (6) and Use in Specific Populations (8.4)].

5.7 Multiple Vertebral Fractures (MVF) Following Treatment Discontinuation

Multiple vertebral fractures (MVF) have been reported following discontinuation of treatment with denosumab. Patients at higher risk for MVF include those with risk factors for or a history of osteoporosis or prior fractures.

When Xgeva treatment is discontinued, evaluate the individual patient’s risk for vertebral fractures [see Patient Counseling Information (17)].

5.8 Embryo-Fetal Toxicity

Based on data from animal studies and its mechanism of action, Xgeva can cause fetal harm when administered to a pregnant woman. In animal reproduction studies, administration of denosumab to cynomolgus monkeys throughout pregnancy at a dose 25-fold higher than the recommended human dose of Xgeva based on body weight resulted in increased fetal loss, stillbirths, and postnatal mortality, along with evidence of absent peripheral lymph nodes, abnormal bone growth and decreased neonatal growth.

Verify the pregnancy status of females of reproductive potential prior to the initiation of Xgeva. Advise pregnant women and females of reproductive potential that exposure to Xgeva during pregnancy or within 5 months prior to conception can result in fetal harm. Advise females of reproductive potential to use effective contraception during therapy, and for at least 5 months after the last dose of Xgeva [see Use in Specific Populations (8.1, 8.3) and Clinical Pharmacology (12.1)].

6 ADVERSE REACTIONS

The following adverse reactions are discussed below and elsewhere in the labeling:

• Hypersensitivity [see Warnings and Precautions (5.2)]

• Hypocalcemia [see Warnings and Precautions (5.3) and Use in Specific Populations (8.6)]

• Osteonecrosis of the Jaw [see Warnings and Precautions (5.4)]

• Atypical Subtrochanteric and Diaphyseal Femoral Fracture [see Warnings and Precautions (5.5)]

• Hypercalcemia following treatment discontinuation in patients with giant cell tumor of bone and in patients with growing skeletons [see Warnings and Precautions (5.6) and Use in Specific Populations (8.4)]

• Multiple vertebral fractures (MVF) following treatment discontinuation [see Warnings and Precautions (5.7)]

6.1 Clinical Trials Experience

Because clinical trials are conducted under widely varying conditions, adverse reaction rates observed in the clinical trials of a drug cannot be directly compared to rates in the clinical trials of another drug and may not reflect the rates observed in practice.

Bone Metastasis from Solid Tumors

The safety of Xgeva was evaluated in three randomized, double-blind, double-dummy trials [see Clinical Trials (14.1)] in which a total of 2841 patients with bone metastasis from prostate cancer, breast cancer, or other solid tumors, or lytic bony lesions from multiple myeloma received at least one dose of Xgeva. In Studies 20050136, 20050244, and 20050103, patients were randomized to receive either 120 mg of Xgeva every 4 weeks as a subcutaneous injection or 4 mg (dose adjusted for reduced renal function) of zoledronic acid every 4 weeks by intravenous (IV) infusion. Entry criteria included serum calcium (corrected) from 8 to 11.5 mg/dL (2 to 2.9 mmol/L) and creatinine clearance 30 mL/min or greater. Patients who had received IV bisphosphonates were excluded, as were patients with prior history of ONJ or osteomyelitis of the jaw, an active dental or jaw condition requiring oral surgery, non-healed dental/oral surgery, or any planned invasive dental procedure. During the study, serum chemistries including calcium and phosphorus were monitored every 4 weeks. Calcium and vitamin D supplementation was recommended but not required.

The median duration of exposure to Xgeva was 12 months (range: 0.1-41) and median duration on-study was 13 months (range: 0.1-41). Of patients who received Xgeva, 46% were female. Eighty-five percent were White, 5% Hispanic/Latino, 6% Asian, and 3% Black. The median age was 63 years (range: 18-93). Seventy-five percent of patients who received Xgeva received concomitant chemotherapy.

The most common adverse reactions in patients (incidence greater than or equal to 25%) were fatigue/asthenia, hypophosphatemia, and nausea (see Table 1). The most common serious adverse reaction was dyspnea. The most common adverse reactions resulting in discontinuation of Xgeva were osteonecrosis and hypocalcemia.

Table 1. Selecteda Adverse Reactions of Any Severity (Studies 20050136, 20050244, and 20050103)
Body System | Xgeva n = 2841 % | Zoledronic Acid n = 2836 %
GASTROINTESTINAL
Nausea | 31 | 32
Diarrhea | 20 | 19
GENERAL
Fatigue/Asthenia | 45 | 46
INVESTIGATIONS
Hypocalcemiab | 18 | 9
Hypophosphatemiab | 32 | 20
NEUROLOGICAL
Headache | 13 | 14
RESPIRATORY
Dyspnea | 21 | 18
Cough | 15 | 15
1. Adverse reactions reported in at least 10% of patients receiving Xgeva in Studies 20050136, 20050244, and 20050103, and meeting one of the following criteria:
  - At least 1% greater incidence in Xgeva-treated patients, or
  - Between-group difference (either direction) of less than 1% and more than 5% greater incidence in patients treated with zoledronic acid compared to placebo (US Prescribing Information for zoledronic acid)
2. Laboratory-derived and below the central laboratory lower limit of normal [8.3 - 8.5 mg/dL (2.075 - 2.125 mmol/L) for calcium and 2.2 - 2.8 mg/dL (0.71 - 0.9 mmol/L) for phosphorus]

Severe Mineral/Electrolyte Abnormalities

▪ Severe hypocalcemia (corrected serum calcium less than 7 mg/dL or less than 1.75 mmol/L) occurred in 3.1% of patients treated with Xgeva and 1.3% of patients treated with zoledronic acid. Of patients who experienced severe hypocalcemia, 33% experienced 2 or more episodes of severe hypocalcemia and 16% experienced 3 or more episodes [see Warnings and Precautions (5.3) and Use in Specific Populations (8.6)].

▪ Severe hypophosphatemia (serum phosphorus less than 2 mg/dL or less than 0.6 mmol/L) occurred in 15% of patients treated with Xgeva and 7% of patients treated with zoledronic acid.

Osteonecrosis of the Jaw (ONJ)

In the primary treatment phases of Studies 20050136, 20050244, and 20050103, ONJ was confirmed in 1.8% of patients in the Xgeva group (median exposure of 12.0 months; range: 0.1-41) and 1.3% of patients in the zoledronic acid group. The trials in patients with breast (Study 20050136) or prostate (Study 20050103) cancer included an Xgeva open-label extension treatment phase where patients were offered Xgeva 120 mg once every 4 weeks (median overall exposure of 14.9 months; range: 0.1-67.2). The patient-year adjusted incidence (number of events per 100 patient years) of confirmed ONJ was 1.1% during the first year of treatment, 3.7% in the second year, and 4.6% per year thereafter. The median time to ONJ was 20.6 months (range: 4-53) [see Warnings and Precautions (5.4)].

In a placebo-controlled clinical trial with an extension treatment phase evaluating Xgeva for the prevention of bone metastases in patients with non-metastatic prostate cancer (a patient population for which Xgeva is not indicated), with longer treatment exposure of up to 7 years, the patient-year adjusted incidence (number of events per 100 patient years) of confirmed ONJ was 1.1% during the first year of treatment, 3% in the second year, and 7% per year thereafter.

Atypical Subtrochanteric and Diaphyseal Fracture

In the clinical trial program, atypical femoral fracture has been reported in patients treated with Xgeva and the risk increased with longer duration of treatment. Events have occurred during treatment and after treatment was discontinued [see Warnings and Precautions (5.5)].

Multiple Myeloma

The safety of Xgeva was evaluated in an international, randomized (1:1), double-blind, active-controlled trial of patients with newly diagnosed multiple myeloma with treatment through disease progression [see Clinical Trials (14.2)]. In this trial, patients received 120 mg Xgeva every 4 weeks as a subcutaneous injection (n = 850) or 4 mg (dose adjusted for renal function) of zoledronic acid intravenously (IV) every 4 weeks by IV infusion (n = 852). Entry criteria included serum calcium (corrected) from 8 to 11.5 mg/dL (2 to 2.9 mmol/L) and creatinine clearance 30 mL/min or greater. Patients who had received IV bisphosphonates were excluded, as were patients with prior history of ONJ or osteomyelitis of the jaw, an active dental or jaw condition requiring oral surgery, non-healed dental/oral surgery, or any planned invasive dental procedure. During the study, serum chemistries including calcium and phosphorus were monitored every 4 weeks. Calcium and vitamin D supplementation was recommended but not required.

The median duration of exposure to Xgeva was 16 months (range: 1-50) and median duration on-study was 17 months (range: 0-49). Of patients who received Xgeva, 46% were female, 83% percent were White, 13% Asian, 3% Black or African American, and 4% Hispanic/Latino. The median age of the patients randomized to Xgeva was 63 years (range: 29-91) and all patients who received Xgeva received concomitant anti-myeloma chemotherapy.

The adverse reaction profile of Xgeva in patients with multiple myeloma, Study 20090482, was similar to that observed in Studies 20050136, 20050244, and 20050103. The most common adverse reactions (incidence ≥ 10%) were diarrhea (34%), nausea (32%), anemia (22%), back pain (21%), thrombocytopenia (19%), peripheral edema (17%), hypocalcemia (16%), upper respiratory tract infection (15%), rash (14%), and headache (11%). The most common serious adverse reaction (incidence ≥ 5%) was pneumonia (8%). The most common adverse reaction resulting in discontinuation of Xgeva (≥ 1%) was osteonecrosis of the jaw.

Hypocalcemia and Hypophosphatemia

Severe hypocalcemia (corrected serum calcium less than 7 mg/dL or less than 1.75 mmol/L) and severe hypophosphatemia (serum phosphorus less than 2 mg/dL or less than 0.6 mmol/L) occurred in 2% and 21% patients treated with Xgeva, respectively.

Osteonecrosis of the Jaw (ONJ)

In the primary treatment phase of Study 20090482, ONJ was confirmed in 4.1% of patients in the Xgeva group (median exposure of 16 months; range: 1-50) and 2.8% of patients in the zoledronic acid group (median 15 months, range: 1-45 months). At the completion of the double-blind treatment phase of Study 20090482, the patient-year adjusted incidence (number of events per 100 patient years) of confirmed ONJ in the Xgeva group (median exposure of 19.4 months; range: 1-52) was 2% during the first year of treatment, 5% in the second year, and 4.5% per year thereafter. The median time to ONJ was 18.7 months (range: 1-44) [see Warnings and Precautions (5.4)].

Giant Cell Tumor of Bone

The safety of Xgeva was evaluated in two single-arm trials (Study 20062004 and Study 20040215) [see Clinical Trials (14.3)] in which a total of 548 adult or skeletally mature adolescent patients with giant cell tumor of bone received at least 1 dose of Xgeva. Patients received 120 mg Xgeva subcutaneously every 4 weeks with additional 120 mg doses on Days 8 and 15 of the first month of therapy. Patients receiving concurrent bisphosphonate therapy were excluded from enrollment in both studies. Patients with prior history of ONJ or osteomyelitis of the jaw, an active dental or jaw condition requiring oral surgery, non-healed dental/oral surgery, or any planned invasive dental procedure were excluded from enrollment in Study 20040215. During the trial, serum chemistries including calcium and phosphorus were monitored every 4 weeks. Calcium and vitamin D supplementation was recommended but not required.

Of the 548 patients who received Xgeva, 467 patients were treated with Xgeva for ≥ 1 year, 323 patients for ≥ 2 years, and 255 patients for ≥ 3 years. The median number of doses received was 33 (range: 4-138 doses) and the median number of months on-study was 60 (range: 0-140 months). Fifty-seven percent of the enrolled patients were women and 82% were White. The median age was 33 years (range: 13-83 years); a total of 19 patients were skeletally mature adolescents (12 to <17 years of age).

The common adverse reaction profile of Xgeva in patients with giant cell tumor of bone was generally similar to that reported in Studies 20050136, 20050244, and 20050103. The most common adverse reactions in patients (incidence ≥ 10%) were arthralgia, back pain, pain in extremity, fatigue, headache, nausea, nasopharyngitis, musculoskeletal pain, toothache, vomiting, hypophosphatemia, constipation, diarrhea, and cough. The most frequent serious adverse reactions were osteonecrosis of the jaw (3.6%), bone giant cell tumor (1.5%), anemia (1.1%), pneumonia (0.9%), and back pain (0.9%). The most frequent adverse reactions resulting in discontinuation of Xgeva was osteonecrosis of the jaw (incidence of 3.6%). The adverse reaction profile appeared similar in skeletally mature adolescents and adults.

Hypocalcemia and Hypophosphatemia

- Moderate to severe hypocalcemia (corrected serum calcium less than 8 mg/dL or less than 2 mmol/L) occurred in 5% of patients treated with Xgeva.
- Severe hypophosphatemia (serum phosphorus less than 2 to 1 mg/dL or less than 0.6 to 0.3 mmol/L) occurred in 20% of patients treated with Xgeva.

Osteonecrosis of the Jaw (ONJ)

In the pooled analysis of Study 20062004 and Study 20040215, ONJ was confirmed in 7% of patients who received Xgeva (median number of doses received: 33; range: 4-138 doses).

Study 20140114 (NCT03301857) was a 5-year long term follow-up study for patients (n = 85) who completed Study 20062004. In Study 20062004 and Study 20140114 combined, ONJ was confirmed in 7% of patients who received Xgeva (median time on trial 62.2 months (range 0 - 173). The combined patient-year adjusted incidence (number of events per 100 patient years) of confirmed ONJ was 0.2% during the first year of treatment, 1.5% in the second year, 1.8% in the third year, 2.1% in the fourth year, 1.4% in the fifth year, and 1.5% thereafter [see Warnings and Precautions (5.4)].

Atypical Subtrochanteric and Diaphyseal Fracture

In the pooled analysis of Study 20062004 and Study 20040215, atypical femoral fracture was observed in 0.9% of patients who received Xgeva (median number of doses received: 33; range: 4-138 doses).

In Study 20062004 and Study 20140114, the combined incidence of confirmed atypical femoral fracture was 1.3% of patients who received Xgeva [see Warnings and Precautions (5.5)].

Hypercalcemia Following Treatment Discontinuation

In the pooled safety population, 0.7% of patients experienced serious adverse events of hypercalcemia > 30 days following treatment discontinuation that was recurrent in some patients [see Warnings and Precautions (5.6)].

Hypercalcemia of Malignancy

Xgeva was evaluated in an open-label, single-arm trial (Study 20070315) in which 33 patients with hypercalcemia of malignancy (with or without bone metastases) refractory to treatment with intravenous bisphosphonate therapy were enrolled [see Clinical Trials (14.4)].

The adverse reaction profile of Xgeva in patients with hypercalcemia of malignancy was similar to that reported in Studies 20050136, 20050244, 20050103, 20062004, and 20040215. Adverse reactions occurring in greater than 20% of patients were nausea (30%), dyspnea (27%), decreased appetite (24%), headache (24%), peripheral edema (24%), vomiting (24%), anemia (21%), constipation (21%), and diarrhea (21%). The following adverse reactions of Grade 3 or greater severity related to study therapy were reported on-study: fatigue (3%) and infection (6%). Grade 3 laboratory abnormalities included hypomagnesemia (3%), hypokalemia (3%), and hypophosphatemia (76%) of patients. No deaths on-study were related to Xgeva therapy.

6.2 Postmarketing Experience

The following adverse reactions have been identified during post approval use of Xgeva. Because these reactions are reported voluntarily from a population of uncertain size, it is not always possible to reliably estimate their frequency or establish a causal relationship to drug exposure.

- Hypocalcemia: Severe symptomatic hypocalcemia, including fatal cases [see Contraindications (4.1) and Warnings and Precautions (5.3)].
- Hypercalcemia: Severe symptomatic hypercalcemia following treatment discontinuation can occur [see Adverse Reactions (6) and Warnings and Precautions (5.6)].
- Hypersensitivity, including anaphylactic reactions [see Contraindications (4.2) and Warnings and Precautions (5.2)].
- Musculoskeletal pain, including severe musculoskeletal pain. Positive re-challenge has been reported.
- Lichenoid drug eruptions (e.g., lichen planus-like reactions).
- Alopecia.

8 USE IN SPECIFIC POPULATIONS

8.1 Pregnancy

Risk Summary

Based on findings in animals and its mechanism of action, Xgeva can cause fetal harm when administered to a pregnant woman [see Clinical Pharmacology (12.1)]. There are insufficient data with denosumab use in pregnant women to inform any drug associated risks for adverse developmental outcomes. In utero denosumab exposure from cynomolgus monkeys dosed monthly with denosumab throughout pregnancy at a dose 25-fold higher than the recommended human dose of Xgeva based on body weight resulted in increased fetal loss, stillbirths, and postnatal mortality; and absent lymph nodes, abnormal bone growth, and decreased neonatal growth [see Data].

Apprise pregnant women of the potential risk to the fetus.

The background rate of major birth defects and miscarriage is unknown for the indicated population. In the U.S. general population, the estimated background risk of major birth defects and miscarriage in clinically recognized pregnancies is 2-4% and 15-20%, respectively.

Data

Animal Data

The effects of denosumab on prenatal development have been studied in both cynomolgus monkeys and genetically engineered mice in which RANK ligand (RANKL) expression was turned off by gene removal (a “knockout mouse”). In cynomolgus monkeys dosed subcutaneously with denosumab throughout pregnancy starting at gestational day 20 and at a pharmacologically active dose 25-fold higher than the recommended human dose of Xgeva based on body weight, there was increased fetal loss during gestation, stillbirths, and postnatal mortality. Other findings in offspring included absence of axillary, inguinal, mandibular, and mesenteric lymph nodes; abnormal bone growth, reduced bone strength, reduced hematopoiesis, dental dysplasia, and tooth malalignment; and decreased neonatal growth. At birth out to one month of age, infants had measurable blood levels of denosumab (22-621% of maternal levels).

Following a recovery period from birth out to 6 months of age, the effects on bone quality and strength returned to normal; there were no adverse effects on tooth eruption, though dental dysplasia was still apparent; axillary and inguinal lymph nodes remained absent, while mandibular and mesenteric lymph nodes were present, though small; and minimal to moderate mineralization in multiple tissues was seen in one recovery animal. There was no evidence of maternal harm prior to labor; adverse maternal effects occurred infrequently during labor. Maternal mammary gland development was normal. There was no fetal NOAEL (no observable adverse effect level) established for this study because only one dose of 50 mg/kg was evaluated. Mammary gland histopathology at 6 months of age was normal in female offspring exposed to denosumab in utero; however, development and lactation have not been fully evaluated.

In RANKL knockout mice, absence of RANKL (the target of denosumab) also caused fetal lymph node agenesis and led to postnatal impairment of dentition and bone growth. Pregnant RANKL knockout mice showed altered maturation of the maternal mammary gland, leading to impaired lactation [see Use in Specific Populations (8.3) and Nonclinical Toxicology (13.2)].

8.2 Lactation

Risk Summary

There is no information regarding the presence of Xgeva (denosumab) in human milk, the effects on the breastfed child, or the effects on milk production. Denosumab was detected in the maternal milk of cynomolgus monkeys up to 1 month after the last dose of denosumab (≤ 0.5% milk:serum ratio) and maternal mammary gland development was normal, with no impaired lactation. However, pregnant RANKL knockout mice showed altered maturation of the maternal mammary gland, leading to impaired lactation [see Use in Specific Populations (8.1) and Nonclinical Toxicology (13.2)]. Consider the developmental and health benefits of breastfeeding along with the mother’s clinical need for Xgeva treatment and any potential adverse effects on the breastfed child from Xgeva or from the underlying maternal condition.

8.3 Females and Males of Reproductive Potential

Based on findings in animals and its mechanism of action, Xgeva can cause fetal harm when administered to a pregnant woman [see Use in Specific Populations (8.1)].

Pregnancy Testing

Verify the pregnancy status of females of reproductive potential prior to initiating Xgeva treatment.

Contraception

Females

Advise females of reproductive potential to use effective contraception during therapy, and for at least 5 months after the last dose of Xgeva.

8.4 Pediatric Use

The safety and efficacy of Xgeva have not been established in pediatric patients except in skeletally mature adolescents (aged 12–16 years) with giant cell tumor of bone. Xgeva is recommended only for treatment of skeletally mature adolescents (aged 12–16 years) with giant cell tumor of bone [see Indications and Usage (1.2)]. Clinically significant hypercalcemia after treatment discontinuation has been reported in pediatric patients with growing skeletons who received denosumab for giant cell tumor of bone or for unapproved indications [see Adverse Reactions (6.2) and Warnings and Precautions (5.6)].

Xgeva was studied in an open-label trial that enrolled a subset of 19 adolescent patients (aged 12-16 years) with giant cell tumor of bone who had reached skeletal maturity, defined by at least 1 mature long bone (e.g., closed epiphyseal growth plate of the humerus), and had a body weight ≥ 45 kg [see Indications and Usage (1.2) and Clinical Trials (14.3)]. A total of one of five (20%) evaluable adolescent patients had an objective response by retrospective independent assessment of radiographic response according to modified Response Evaluation Criteria in Solid Tumors (RECIST 1.1). The adverse reaction profile and efficacy results appeared to be similar in skeletally mature adolescents and adults [see Adverse Reactions (6.1) and Clinical Trials (14.3)].

Animal Data

Treatment with Xgeva may impair bone growth in children with open growth plates and may inhibit eruption of dentition. In neonatal rats, inhibition of RANKL (the target of Xgeva therapy) with a construct of osteoprotegerin bound to Fc (OPG-Fc) at doses ≤ 10 mg/kg was associated with inhibition of bone growth and tooth eruption. Adolescent primates treated with denosumab at doses 5 and 25 times (10 and 50 mg/kg dose) higher than the recommended human dose of 120 mg administered once every 4 weeks, based on body weight (mg/kg), had abnormal growth plates, considered to be consistent with the pharmacological activity of denosumab.

Cynomolgus monkeys exposed in utero to denosumab exhibited bone abnormalities, reduced hematopoiesis, tooth malalignment, decreased neonatal growth, and an absence of axillary, inguinal, mandibular, and mesenteric lymph nodes. Some bone abnormalities recovered once exposure was ceased following birth; however, axillary and inguinal lymph nodes remained absent 6 months post-birth [see Use in Specific Populations (8.1)].

8.5 Geriatric Use

Of the total number of patients in clinical studies that received Xgeva (n = 2841) in Studies 20050136, 20050244, and 20050103, 1271 (44%) were ≥ 65 years old, while 473 patients (17%) were ≥ 75 years old. Of the 859 patients in Study 20090482 that received Xgeva, 387 patients (45%) were ≥ 65 years old, while 141 patients (16%) were ≥ 75 years old. No overall differences in safety or efficacy were observed between older and younger patients.

8.6 Renal Impairment

Two clinical trials were conducted in patients without cancer and with varying degrees of renal function.

In one study, patients (N = 55) with varying degrees of renal function (ranging from normal through end-stage renal disease requiring dialysis) received a single 60 mg subcutaneous dose of denosumab. In a second study, patients (N = 32) with severe renal dysfunction (creatinine clearance less than 30 mL/min and/or on dialysis) were given two 120 mg subcutaneous doses of denosumab. In both studies, greater risk of developing hypocalcemia was observed with increasing renal impairment, and with inadequate/no calcium supplementation. Hypocalcemia was mild to moderate in severity in 96% of patients. Monitor calcium levels and calcium and vitamin D intake [see Warnings and Precautions (5.3), Adverse Reactions (6.1), and Clinical Pharmacology (12.3)].

10 OVERDOSAGE

There is no experience with overdosage of Xgeva.

11 DESCRIPTION

Denosumab is a human IgG2 monoclonal antibody that binds to human RANKL. Denosumab has an approximate molecular weight of 147 kDa and is produced in genetically engineered mammalian (Chinese hamster ovary) cells.

Xgeva (denosumab) injection is a sterile, preservative-free, clear, colorless to pale yellow solution.

Each single-dose vial contains 1.7 mL solution of 120 mg denosumab, glacial acetic acid (1.8 mg), polysorbate 20 (0.17 mg), sorbitol (78.1 mg), Water for Injection (USP), and sodium hydroxide to adjust the pH to 5.2.

12 CLINICAL PHARMACOLOGY

12.1 Mechanism of Action

Xgeva binds to RANKL, a transmembrane or soluble protein essential for the formation, function, and survival of osteoclasts, the cells responsible for bone resorption, thereby modulating calcium release from bone. Increased osteoclast activity, stimulated by RANKL, is a mediator of bone pathology in solid tumors with osseous metastases. Similarly, giant cell tumors of bone consist of stromal cells expressing RANKL and osteoclast-like giant cells expressing RANK receptor, and signaling through the RANK receptor contributes to osteolysis and tumor growth. Xgeva prevents RANKL from activating its receptor, RANK, on the surface of osteoclasts, their precursors, and osteoclast-like giant cells.

12.2 Pharmacodynamics

In patients with breast cancer and bone metastases, the median reduction in uNTx/Cr was 82% within 1 week following initiation of Xgeva 120 mg administered subcutaneously. In Studies 20050136, 20050244, and 20050103, the median reduction in uNTx/Cr from baseline to Month 3 was approximately 80% in 2075 Xgeva-treated patients.

In a phase 3 study of patients with newly diagnosed multiple myeloma who received subcutaneous doses of Xgeva 120 mg every 4 weeks (Q4W), median reductions in uNTx/Cr of approximately 75% were observed by Week 5. Reductions in bone turnover markers were maintained, with median reductions of 74% to 79% for uNTx/Cr from weeks 9 to 49 of continued 120 mg Q4W dosing.

In adult and skeletally mature adolescent patients with giant cell tumor of bone who received subcutaneous doses of Xgeva 120 mg Q4W with a 120 mg loading dose on Days 8 and 15, median reductions in uNTx/Cr from baseline were 84% at Week 13 and 82% at Week 25.

12.3 Pharmacokinetics

Following subcutaneous administration, bioavailability was 62%. Denosumab displayed nonlinear pharmacokinetics at doses below 60 mg, but approximately dose-proportional increases in exposure at higher doses.

With multiple subcutaneous doses of 120 mg once every 4 weeks, up to 2.8-fold accumulation in serum denosumab concentrations was observed and steady-state was achieved by 6 months. A mean (± standard deviation) serum steady-state trough concentration of 20.5 (± 13.5) mcg/mL was achieved by 6 months. The mean elimination half-life was 28 days.

In patients with newly diagnosed multiple myeloma who received 120 mg every 4 weeks, denosumab concentrations appear to reach steady-state by Month 6. In patients with giant cell tumor of bone, after administration of subcutaneous doses of 120 mg once every 4 weeks with additional 120 mg doses on Days 8 and 15 of the first month of therapy, mean (± standard deviation) serum trough concentrations on Day 8, 15, and one month after the first dose were 19.0 (± 24.1), 31.6 (± 27.3), 36.4 (± 20.6) mcg/mL, respectively. Steady-state was achieved in 3 months after initiation of treatment with a mean serum trough concentration of 23.4 (± 12.1) mcg/mL.

Special Populations

Body Weight: A population pharmacokinetic analysis was performed to evaluate the effects of demographic characteristics. Denosumab clearance and volume of distribution were proportional to body weight. The steady-state exposure following repeat subcutaneous administration of 120 mg every 4 weeks to 45 kg and 120 kg subjects were, respectively, 48% higher and 46% lower than exposure of the typical 66 kg subject.

Age, Gender and Race: The pharmacokinetics of denosumab was not affected by age, gender, and race.

Pediatrics: In skeletally-mature adolescent patients (12 to 16 years of age) with giant cell tumor of bone (GCTB) who received 120 mg every 4 weeks with a 120 mg loading dose on Days 8 and 15, the pharmacokinetics of denosumab were comparable to those observed in adult patients with GCTB.

Hepatic Impairment: No clinical trials have been conducted to evaluate the effect of hepatic impairment on the pharmacokinetics of denosumab.

Renal Impairment: In clinical trials of 87 patients with varying degrees of renal dysfunction, including patients on dialysis, the degree of renal impairment had no effect on the pharmacokinetics and pharmacodynamics of denosumab [see Use in Specific Populations (8.6)].

Drug Interactions

No formal drug-drug interaction trials have been conducted with Xgeva. There was no evidence that various anticancer treatments affected denosumab systemic exposure and pharmacodynamic effect. Serum denosumab concentrations at 1 and 3 months and reductions in the bone turnover marker uNTx/Cr (urinary N-terminal telopeptide corrected for creatinine) at 3 months were similar in patients with and without prior intravenous bisphosphonate therapy and were not altered by concomitant chemotherapy and/or hormone therapy.

12.6 Immunogenicity

The observed incidence of anti-drug antibodies is highly dependent on the sensitivity and specificity of the assay. Differences in assay methods preclude meaningful comparisons of the incidence of anti-drug antibodies in the studies described below with the incidence of anti-drug antibodies in other studies, including those of denosumab or of other denosumab products. Using an electrochemiluminescent bridging immunoassay, less than 1% (55 out of 8113) of patients treated with denosumab for up to 5 years tested positive for binding antibodies (including pre-existing, transient, and developing antibodies). None of the patients tested positive for neutralizing antibodies, as was assessed using a chemiluminescent cell- based in vitro biological assay. There was no identified clinically significant effect of anti-drug antibodies on pharmacokinetics, pharmacodynamics, safety, or effectiveness of denosumab.

13 NONCLINICAL TOXICOLOGY

13.1 Carcinogenesis, Mutagenesis, Impairment of Fertility

Carcinogenicity

The carcinogenic potential of denosumab has not been evaluated in long-term animal studies.

Mutagenicity

The genotoxic potential of denosumab has not been evaluated.

Impairment of Fertility

Denosumab had no effect on female fertility or male reproductive organs in monkeys at doses that were 6.5- to 25-fold higher than the recommended human dose of 120 mg subcutaneously administered once every 4 weeks, based on body weight (mg/kg).

13.2 Animal Toxicology and/or Pharmacology

Denosumab is an inhibitor of osteoclastic bone resorption via inhibition of RANKL.

Because the biological activity of denosumab in animals is specific to nonhuman primates, evaluation of genetically engineered (knockout) mice or use of other biological inhibitors of the RANK/RANKL pathway, OPG-Fc and RANK-Fc, provided additional information on the pharmacodynamic properties of denosumab. RANK/RANKL knockout mice exhibited absence of lymph node formation, as well as an absence of lactation due to inhibition of mammary gland maturation (lobulo-alveolar gland development during pregnancy). Neonatal RANK/RANKL knockout mice exhibited reduced bone growth and lack of tooth eruption. A corroborative study in 2-week-old rats given the RANKL inhibitor OPG-Fc also showed reduced bone growth, altered growth plates, and impaired tooth eruption. These changes were partially reversible in this model when dosing with the RANKL inhibitors was discontinued.

14 CLINICAL TRIALS

14.1 Bone Metastasis from Solid Tumors

The safety and efficacy of Xgeva for the prevention of skeletal-related events in patients with bone metastases from solid tumors was demonstrated in three international, randomized (1:1), double-blind, active-controlled, noninferiority trials comparing Xgeva with zoledronic acid. In all three trials, patients were randomized to receive 120 mg Xgeva subcutaneously every 4 weeks or 4 mg zoledronic acid intravenously (IV) every 4 weeks (dose adjusted for reduced renal function). Patients with creatinine clearance less than 30 mL/min were excluded. In each trial, the main outcome measure was demonstration of noninferiority of time to first skeletal-related event (SRE) as compared to zoledronic acid. Supportive outcome measures were superiority of time to first SRE and superiority of time to first and subsequent SRE; testing for these outcome measures occurred if the main outcome measure was statistically significant. An SRE was defined as any of the following: pathologic fracture, radiation therapy to bone, surgery to bone, or spinal cord compression.

Study 20050136 (NCT00321464) enrolled 2046 patients with advanced breast cancer and bone metastasis. Randomization was stratified by a history of prior SRE (yes or no), receipt of chemotherapy within 6 weeks prior to randomization (yes or no), prior oral bisphosphonate use (yes or no), and region (Japan or other countries). Forty percent of patients had a previous SRE, 40% received chemotherapy within 6 weeks prior to randomization, 5% received prior oral bisphosphonates, and 7% were enrolled from Japan. Median age was 57 years, 80% of patients were White, and 99% of patients were women. The median number of doses administered was 18 for denosumab and 17 for zoledronic acid.

Study 20050244 (NCT00330759) enrolled 1776 adults with solid tumors other than breast and castrate-resistant prostate cancer with bone metastasis and multiple myeloma. Randomization was stratified by previous SRE (yes or no), systemic anticancer therapy at time of randomization (yes or no), and tumor type (non-small cell lung cancer, myeloma, or other). Eighty-seven percent were receiving systemic anticancer therapy at the time of randomization, 52% had a previous SRE, 64% of patients were men, 87% were White, and the median age was 60 years. A total of 40% of patients had non-small cell lung cancer, 10% had multiple myeloma, 9% had renal cell carcinoma, and 6% had small cell lung cancer. Other tumor types each comprised less than 5% of the enrolled population. The median number of doses administered was 7 for both denosumab and zoledronic acid.

Study 20050103 (NCT00321620) enrolled 1901 men with castrate-resistant prostate cancer and bone metastasis. Randomization was stratified by previous SRE, PSA level (less than 10 ng/mL or 10 ng/mL or greater) and receipt of chemotherapy within 6 weeks prior to randomization (yes or no). Twenty-six percent of patients had a previous SRE, 15% of patients had PSA less than 10 ng/mL, and 14% received chemotherapy within 6 weeks prior to randomization. Median age was 71 years and 86% of patients were White. The median number of doses administered was 13 for denosumab and 11 for zoledronic acid.

Xgeva delayed the time to first SRE following randomization as compared to zoledronic acid in patients with breast or castrate-resistant prostate cancer (CRPC) with osseous metastases (Table 2). In patients with bone metastasis due to other solid tumors or lytic lesions due to multiple myeloma, Xgeva was noninferior to zoledronic acid in delaying the time to first SRE following randomization.

Overall survival and progression-free survival were similar between arms in all three trials.

Table 2. Efficacy Results for Xgeva Compared to Zoledronic Acid
 | Study 20050136 Metastatic Breast Cancer |  |  |  | Study 20050244 Metastatic Solid Tumors or Multiple Myeloma |  |  |  | Study 20050103 Metastatic CRPCa
 | Xgeva N = 1026 |  | Zoledronic Acid N = 1020 |  | Xgeva N = 886 |  | Zoledronic Acid N = 890 |  | Xgeva N = 950 |  | Zoledronic Acid N = 951
First On-study SRE
Number of Patients who had SREs (%) | 315 (30.7) |  | 372 (36.5) |  | 278 (31.4) |  | 323 (36.3) |  | 341 (35.9) |  | 386 (40.6)
Components of First SRE
Radiation to Bone | 82 (8.0) | 119 (11.7) |  | 119 (13.4) |  | 144 (16.2) |  | 177 (18.6) |  | 203 (21.3)
Pathological Fracture | 212 (20.7) | 238 (23.3) |  | 122 (13.8) |  | 139 (15.6) |  | 137 (14.4) |  | 143 (15.0)
Surgery to Bone | 12 (1.2) | 8 (0.8) |  | 13 (1.5) |  | 19 (2.1) |  | 1 (0.1) |  | 4 (0.4)
Spinal Cord Compression | 9 (0.9) | 7 (0.7) |  | 24 (2.7) |  | 21 (2.4) |  | 26 (2.7) |  | 36 (3.8)
Median Time to SRE (months) | NRb | 26.4 |  | 20.5 |  | 16.3 |  | 20.7 |  | 17.1
Hazard Ratio (95% CI) | 0.82 (0.71, 0.95) |  |  | 0.84 (0.71, 0.98) |  |  |  | 0.82 (0.71, 0.95)
Noninferiority p-value | < 0.001 |  |  | < 0.001 |  |  |  | < 0.001
Superiority p-valuec | 0.010 |  |  | 0.060 |  |  |  | 0.008
First and Subsequent SREd
Mean Number/Patient | 0.46 |  | 0.60 |  | 0.44 |  | 0.49 |  | 0.52 |  | 0.61
Rate Ratio (95% CI) | 0.77 (0.66, 0.89) |  |  |  | 0.90 (0.77, 1.04) |  |  |  | 0.82 (0.71, 0.94)
Superiority p-valuee | 0.001 |  |  |  | 0.145 |  |  |  | 0.009
a CRPC = castrate-resistant prostate cancer.
b NR = not reached.
c Superiority testing performed only after denosumab demonstrated to be noninferior to zoledronic acid within trial.
d All skeletal events post randomization; new events defined by occurrence ≥ 21 days after preceding event.
e Adjusted p-values are presented.

14.2 Multiple Myeloma

The efficacy of Xgeva for the prevention of skeletal-related events in newly diagnosed multiple myeloma patients with treatment through disease progression, was evaluated in Study 20090482 (NCT01345019), an international, randomized (1:1), double-blind, active-controlled, noninferiority trial comparing Xgeva with zoledronic acid. In this trial, patients were randomized to receive 120 mg Xgeva subcutaneously every 4 weeks or 4 mg zoledronic acid intravenously (IV) every 4 weeks (dose adjusted for reduced renal function). Patients with creatinine clearance less than 30 mL/min were excluded. In this trial, the main efficacy outcome measure was noninferiority of time to first skeletal-related event (SRE). Additional efficacy outcome measures were superiority of time to first SRE, time to first and subsequent SRE, and overall survival. An SRE was defined as any of the following: pathologic fracture, radiation therapy to bone, surgery to bone, or spinal cord compression.

Study 20090482 enrolled 1718 newly diagnosed multiple myeloma patients with bone lesions. Randomization was stratified by a history of prior SRE (yes or no), the anti-myeloma agent being utilized/planned to be utilized in first-line therapy (novel therapy-based or non-novel therapy-based [novel therapies include bortezomib, lenalidomide, or thalidomide]), intent to undergo autologous PBSC transplantation (yes or no), stage at diagnosis (International Staging System I or II or III) and region Japan (yes or no). At study enrollment, 96% of the patients were receiving or planning to receive novel therapy-based first-line anti-myeloma therapy, 55% of the patients intended to undergo autologous PBSC transplantation, 61% of patients had a previous SRE, 32% were at ISS Stage I, 38% were at ISS Stage II and 29% were at ISS Stage III, and 2% were enrolled from Japan. Median age was 63 years, 82% of patients were White, and 46% of patients were women. The median number of doses administered was 16 for Xgeva and 15 for zoledronic acid.

Xgeva was noninferior to zoledronic acid in delaying the time to first SRE following randomization (HR = 0.98, 95% CI, 0.85-1.14). The results for overall survival (OS) were comparable between Xgeva and zoledronic acid treatment groups with a hazard ratio of 0.90 (95% CI: 0.70, 1.16).

Table 3. Efficacy Results for Xgeva Compared to Zoledronic Acid
 | Study 20090482 Multiple Myeloma
 | Xgeva N = 859 | Zoledronic Acid N = 859
First On-study SRE
Number of Patients who had SREs (%) | 376 (43.8) | 383 (44.6)
Components of First SRE
Radiation to Bone | 47 (5.5) | 62 (7.2)
Pathological Fracture | 342 (39.8) | 338 (39.3)
Surgery to Bone | 37 (4.3) | 48 (5.6)
Spinal Cord Compression | 6 (0.7) | 4 (0.5)
Median Time to SRE (months) (95% CI) | 22.8 (14.7, NEa) | 24 (16.6, 33.3)
Hazard Ratio (95% CI) | 0.98 (0.85, 1.14)
a NE = not estimable

14.3 Giant Cell Tumor of Bone

The safety and efficacy of Xgeva for the treatment of giant cell tumor of bone in adults or skeletally mature adolescents were demonstrated in two open-label trials [Study 20040215 (NCT00396279) and Study 20062004 (NCT00680992)] that enrolled patients with histologically confirmed measurable giant cell tumor of bone that was either recurrent, unresectable, or for which planned surgery was likely to result in severe morbidity. Patients received 120 mg Xgeva subcutaneously every 4 weeks with a loading dose on Days 8 and 15 of the first cycle of therapy. Patients who discontinued Xgeva then entered the safety follow-up phase for a minimum of 60 months. Retreatment with Xgeva while in safety follow-up was allowed for patients who initially demonstrated a response to Xgeva (e.g., in the case of recurrent disease).

Study 20040215 was a single-arm, pharmacodynamic, and proof of concept trial conducted in 37 adult patients with unresectable or recurrent giant cell tumor of bone. Patients were required to have histologically confirmed giant cell tumor of bone and radiologic evidence of measurable disease from a computed tomography (CT) or magnetic resonance imaging (MRI) obtained within 28 days prior to study enrollment. Patients enrolled in Study 20040215 underwent CT or MRI assessment of giant cell tumor of bone at baseline and quarterly during Xgeva treatment.

Study 20062004 was a parallel-cohort, proof of concept, and safety trial conducted in 535 adult or skeletally mature adolescent patients with histologically confirmed giant cell tumor of bone and evidence of measurable active disease. Study 20062004 enrolled 19 patients who were 12-16 years of age [see Use in Specific Populations (8.4)]. Patients enrolled into one of three cohorts: Cohort 1 enrolled 268 patients with surgically unsalvageable disease (e.g., sacral or spinal sites of disease, or pulmonary metastases); Cohort 2 enrolled 252 patients with surgically salvageable disease where the investigator determined that the planned surgery was likely to result in severe morbidity (e.g., joint resection, limb amputation, or hemipelvectomy); Cohort 3 enrolled 15 patients who previously participated in Study 20040215. Patients underwent imaging assessment of disease status at intervals determined by their treating physician.

A retrospective interim analysis concluded by an independent review committee evaluated objective response in 187 patients enrolled and treated in Study 20040215 and Study 20062004 for whom baseline and at least one post-baseline radiographic assessment were available (27 of 37 patients enrolled in Study 20040215 and 160 of 270 patients enrolled in Cohorts 1 and 2 of Study 20062004). The primary efficacy outcome measure was objective response rate using Response Evaluation Criteria in Solid Tumors (RECIST) v 1.1.

The overall objective response rate (RECIST 1.1) was 25% (95% CI: 19, 32). All responses were partial responses. The estimated median time to response was 3 months. In the 47 patients with an objective response, the median duration of follow-up was 20 months (range: 2-44 months), and 51% (24/47) had a duration of response lasting at least 8 months. Three patients experienced disease progression following an objective response.

14.4 Hypercalcemia of Malignancy

The safety and efficacy of Xgeva was demonstrated in an open-label, single-arm trial [Study 20070315 (NCT00896454)] that enrolled 33 patients with hypercalcemia of malignancy (with or without bone metastases) refractory to treatment with intravenous bisphosphonate therapy. Patients received Xgeva subcutaneously every 4 weeks with additional 120 mg doses on Days 8 and 15 of the first month of therapy.

In this trial, refractory hypercalcemia of malignancy was defined as an albumin-corrected calcium of > 12.5 mg/dL (3.1 mmol/L) despite treatment with intravenous bisphosphonate therapy in 7-30 days prior to initiation of Xgeva therapy. The primary outcome measure was the proportion of patients achieving a response, defined as corrected serum calcium (CSC) ≤ 11.5 mg/dL (2.9 mmol/L), within 10 days after Xgeva administration. Efficacy data are summarized in Figure 1 and Table 4. Concurrent chemotherapy did not appear to affect response to Xgeva.

Table 4. Efficacy in Patients with Hypercalcemia of Malignancy Refractory to Bisphosphonate Therapy
 | N = 33 | Proportion (%) (95% CI)
All Responders (CSC ≤ 11.5 mg/dL) by Day 10 | 21 | 63.6
 |  | (45.1, 79.6)
All Responders by Day 57 | 23 | 69.7
 |  | (51.3, 84.4)
Complete Responders (CSC ≤ 10.8 mg/dL) by Day 10 | 12 | 36.4
 |  | (20.4, 54.9)
All Complete Responders by Day 57 | 21 | 63.6
 |  | (45.1, 79.6)

Median time to response (CSC ≤ 11.5 mg/dL) was 9 days (95% CI: 8, 19), and the median duration of response was 104 days (95% CI: 7, not estimable). Median time to complete response (CSC ≤ 10.8 mg/dL) was 23 days (95% CI: 9, 36), and the median duration of complete response was 34 days (95% CI: 1, 134).

16 HOW SUPPLIED/STORAGE AND HANDLING

Xgeva (denosumab) injection is a clear, colorless to pale yellow solution supplied in a single-dose vial.

120 mg/1.7 mL (70 mg/mL) | 1 vial per carton | NDC 55513-730-01 NDC 55513-730-21

Store Xgeva refrigerated at 2°C to 8°C (36°F to 46°F) in the original carton to protect from light. Do not freeze. Prior to administration, Xgeva may be allowed to reach room temperature up to 25°C (77°F) in the original container. Once removed from the refrigerator, Xgeva must not be exposed to temperatures above 25°C (77°F) and must be used within 30 days. Discard Xgeva if not used within the 30 days. Do not use Xgeva after the expiry date printed on the label.

Protect Xgeva from direct light and heat.

Avoid vigorous shaking of Xgeva.

17 PATIENT COUNSELING INFORMATION

Drug Products with Same Active Ingredient

Advise patients that if they receive Xgeva, they should not receive other denosumab products concomitantly [see Warnings and Precautions (5.1)].

Hypersensitivity

Advise patients to seek prompt medical attention if signs or symptoms of hypersensitivity reactions occur. Advise patients who have had signs or symptoms of systemic hypersensitivity reactions that they should not receive denosumab products [see Warnings and Precautions (5.2) and Contraindications (4.2)].

Hypocalcemia

Adequately supplement patients with calcium and vitamin D and instruct them on the importance of maintaining serum calcium levels while receiving Xgeva [see Warnings and Precautions (5.3) and Use in Specific Populations (8.6)]. Advise patients to seek prompt medical attention if they develop signs or symptoms of hypocalcemia.

Osteonecrosis of the Jaw

Advise patients to maintain good oral hygiene during treatment with Xgeva and to inform their dentist prior to dental procedures that they are receiving Xgeva. Patients should avoid invasive dental procedures during treatment with Xgeva and inform their healthcare provider or dentist if they experience persistent pain and/or slow healing of the mouth or jaw after dental surgery [see Warnings and Precautions (5.4)].

Atypical Subtrochanteric and Diaphyseal Femoral Fracture

Advise patients to report new or unusual thigh, hip, or groin pain [see Warnings and Precautions (5.5)].

Hypercalcemia Following Treatment Discontinuation in Patients with Giant Cell Tumor of Bone and in Patients with Growing Skeletons

Advise patients to report nausea, vomiting, headache, and decreased alertness following treatment discontinuation [see Warnings and Precautions (5.6) and Use in Specific Populations (8.4)].

Multiple Vertebral Fractures (MVF) Following Treatment Discontinuation

Advise patients that after treatment with Xgeva is stopped there may be an increased risk of having broken bones in the spine especially in patients who have had a fracture or who have had osteoporosis. Advise patients not to interrupt Xgeva therapy without their physician’s advice [see Warnings and Precautions (5.7)].

Embryo-Fetal Toxicity

Advise females of reproductive potential that Xgeva can cause harm to a fetus and to inform their healthcare provider of a known or suspected pregnancy [see Warnings and Precautions (5.8) and Use in Specific Populations (8.1, 8.3)].

Advise females of reproductive potential to use effective contraception during treatment and for at least 5 months after the last dose of Xgeva [see Use in Specific Populations (8.3)].

Xgeva® (denosumab)

Manufactured by:
Amgen Inc.
One Amgen Center Drive
Thousand Oaks, California 91320-1799
U.S. License No. 1080

Patent: http://pat.amgen.com/xgeva/

© 2010-2020, 2025 Amgen Inc. All rights reserved.

1xxxxx – v23

PRINCIPAL DISPLAY PANEL - 1.7 mL Vial Carton

AMGEN®

120
mg/1.7mL

1 x Single-Dose Vial
NDC 55513-730-01

XGEVA®
(denosumab)

Injection
120 mg/1.7 mL (70 mg/mL)
For Subcutaneous Use Only
Single-Dose Vial. Discard Unused Portion.

Xgeva should be administered by healthcare
provider.

Rx Only